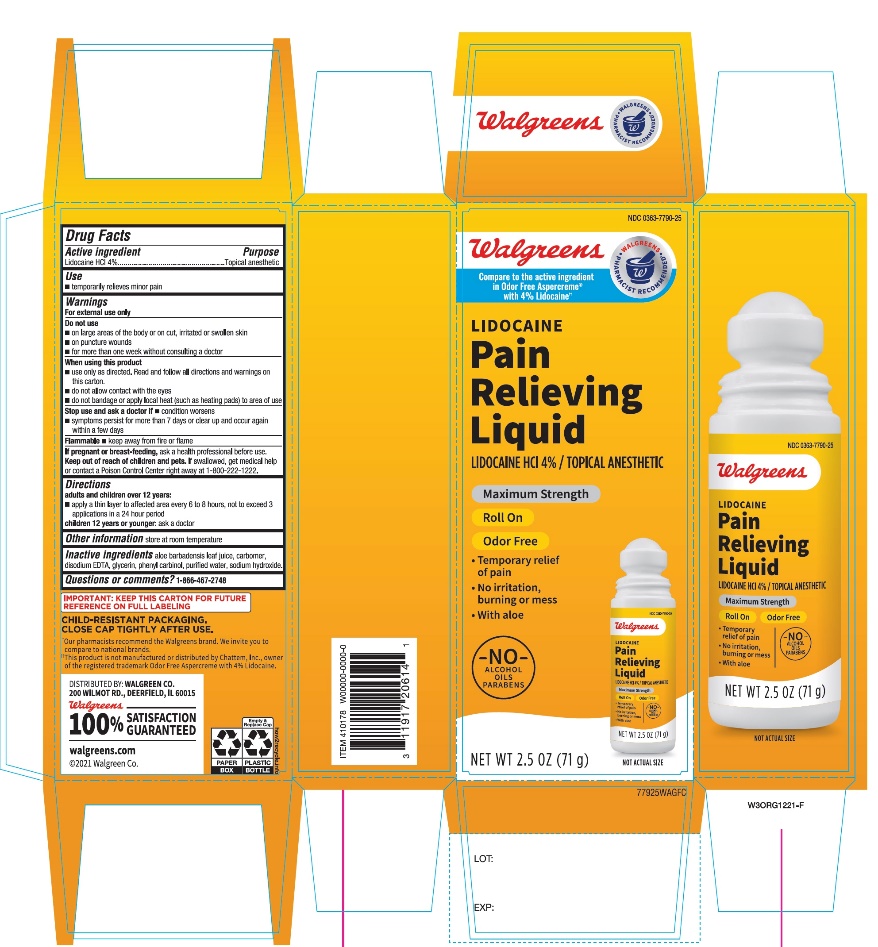 DRUG LABEL: Walgreen Pain Relieving

NDC: 0363-7790 | Form: LIQUID
Manufacturer: WALGREENS CO.
Category: otc | Type: HUMAN OTC DRUG LABEL
Date: 20251126

ACTIVE INGREDIENTS: LIDOCAINE HYDROCHLORIDE 4 g/100 g
INACTIVE INGREDIENTS: ALOE VERA LEAF; CARBOMER COPOLYMER TYPE B (ALLYL PENTAERYTHRITOL CROSSLINKED); EDETATE DISODIUM; GLYCERIN; BENZYL ALCOHOL; WATER; SODIUM HYDROXIDE

Walgreen Maximum Strength Pain Relieving Liquid + Lidocaine

Active ingredient

Lidocaine HCI 4%

Purpose

Topical anesthetic

Uses

- temporarily relieves minor pain

Warnings

For external use only

Do not use

- on large areas of the body or on cut, irritated or swollen skin
- on puncture wounds
- for more than one week without consulting a doctor

When using this product

- use only as directed. Read and follow all directions and warnings on this carton.
- do not allow contact with the eyes
- do not bandage or apply local heat (such as heating pads) to the area of use

Stop use and ask a doctor if

- condition worsens
- symptoms persist for more than 7 days or clear up and occur again within a few days

Flammable

- Keep away from fire or flame

If pregnant or breast-feeding,

ask a health professional before use.

Keep out of reach of children and pets.

If swallowed, get medical help or contact a Poison Control Center right away at 1-800-222-1222.

Directions

adults and children over 12 years:

- apply a thin layer to affected area every 6 to 8 hours, not to exceed 3 applications in a 24 hour period

children 12 years and younger: ask a doctor

Inactive ingredients

aloe barbadensis leaf juice. Carbomer, disodium EDTA, glycerin, phenyl carbinol, purified water, sodium hydroxide.

Questions or comments?

1-866-467-2748

PRINCIPAL DISPLAY PANEL

NDC# 0363-7790-25

Compare to Odor Free Aspercreme® with 4% Lidocaine active ingredient††

FRAGRANCE FREE

Pain Relieving Liquid + Lidocaine

4% LIDOCAINE HCl/TOPICAL ANALGESIC

ROLL ON

MAXIMUM STRENGTH

NON-GREASY

- Temporary relief of pain
- No irritation, burning or mess
- Oil free, paraben free and alcohol-Free

NET WT 2.5 OZ (71 g)

CHILD-RESISTANT PACKAGING. CLOSE CAP TIGHTLY AFTER USE.

Walgreens Trusted since 1901™

PHARMACIST RECOMMENDED†

Health expertise you rely on™.

DISTRIBUTED BY

WALGREEN CO.

200 WILMOT RD., DEERFIELD, IL 60015

Walgreens 100% SATISFACTION GUARANTEED

††Walgreens Pharmacist Survey

walgreens.com

© Walgreen Co.

††This product is not manufactured or distributed by Chattem, Inc., owner of the registered trademark Aspercreme® Odor Free with 4% Lidocaine.